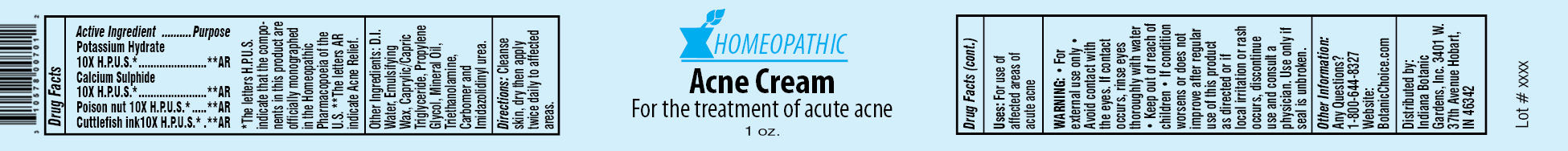 DRUG LABEL: Homeopathic Acne
NDC: 10578-007 | Form: CREAM
Manufacturer: Indiana Botanic Gardens
Category: homeopathic | Type: HUMAN OTC DRUG LABEL
Date: 20120427

ACTIVE INGREDIENTS: CAUSTICUM 10 [hp_X]/28 g; CALCIUM SULFIDE 10 [hp_X]/28 g; STRYCHNOS NUX-VOMICA SEED 10 [hp_X]/28 g; SEPIA OFFICINALIS JUICE 10 [hp_X]/28 g
INACTIVE INGREDIENTS: WATER; CETOSTEARYL ALCOHOL; POLYSORBATE 60; TRICAPRYLIN; PROPYLENE GLYCOL; MINERAL OIL; TROLAMINE; CARBOMER 934; IMIDUREA

Homeopathic Acne Cream

Active Ingredients

Potassium Hydrate 10X H.P.U.S.*

Calcium Sulphide 10X H.P.U.S.*

Poison nut 10X H.P.U.S.*

Cuttlefish ink10X H.P.U.S.*

Purpose

**AR

**AR

**AR

**AR

*The letters H.P.U.S. indicate that the components in this product are officially monographed in the Homeopathic Pharmacopoeia of the U.S. **The letters AR indicate Acne Relief.

Other Ingredients:

D.I. Water, Emulsifying Wax, Caprylic/Capric Triglyceride, Propylene Glycol, Mineral Oil, Triethanolamine, Carbomer and Imidazolidinyl urea.

Directions:

Cleanse skin, dry then apply twice daily to affected areas.

Uses:

For use of affected areas of acute acne

WARNING:

- for external use only
- Avoid contact with the eyes. If contact occurs, rinse eyes thoroughly with water

- Keep out of reach of children

STOP USE

- If condition worsens or does not improve after regular use of this product as directed or if local irritation or rash occurs, discontinue use and consult a physician.

Use only if seal is unbroken.

Other Information:

Any Questions?

1-800-644-8327

Website:

BotanicChoice.com

Distributed by:

Indiana Botanic Gardens, Inc. 3401 W. 37th Avenue Hobart, IN 46342

Homeopathic Acne Cream

For the treatment of acute acne

1 oz.